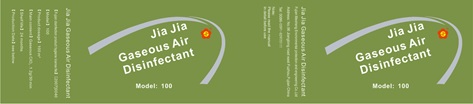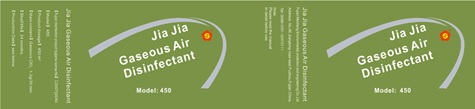 DRUG LABEL: Jiajia Gaseous Air Disinfectant
NDC: 82327-101 | Form: SPRAY
Manufacturer: Fujian Meisheng Environmental protection Co.,Ltd
Category: otc | Type: HUMAN OTC DRUG LABEL
Date: 20211014

ACTIVE INGREDIENTS: CHLORINE DIOXIDE 32 mg/1 g
INACTIVE INGREDIENTS: SODIUM CHLORIDE; WATER

Jiajia Gaseous Air Disinfectant

Active Ingredient(s)

chlorine dioxide 32mg/g. Purpose: Antiseptic

Purpose

Antiseptic, Jiajia Gaseous Air Disinfectant

Use

Jiajia Gaseous Air Disinfectant to help reduce bacteria that potentially can cause disease. For use when soap and water are not available.

Warnings

For external use only.

Do not use

- in children less than 2 months of age
- on open skin wounds

When using this product keep out of eyes, ears, and mouth. In case of contact with eyes, rinse eyes thoroughly with water.
Stop use and ask a doctor if irritation or rash occurs. These may be signs of a serious condition.
Keep out of reach of children. If swallowed, get medical help or contact a Poison Control Center right away.

Stop use and ask a doctor if irritation or rash occurs. These may be signs of a serious condition.

Keep out of reach of children. If swallowed, get medical help or contact a Poison Control Center right away.

Directions

- Spray on the surface of the skin and let it dry naturally
- Supervise children under 6 years of age when using this product to avoid swallowing.

Other information

- Store between 15-30C (59-86F)
- Avoid freezing and excessive heat above 40C (104F)

Inactive ingredients

Sodium chloride
Water